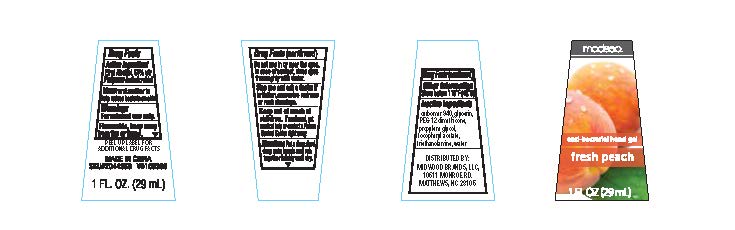 DRUG LABEL: Modesa anti-bacterial hand gel
                
NDC: 58194-001 | Form: GEL
Manufacturer: Shanghai Weierya Daily Chemicals Factory
Category: otc | Type: HUMAN OTC DRUG LABEL
Date: 20130416

ACTIVE INGREDIENTS: ALCOHOL 65 mL/100 mL
INACTIVE INGREDIENTS: CARBOMER HOMOPOLYMER TYPE C (ALLYL PENTAERYTHRITOL CROSSLINKED); GLYCERIN; PEG-12 DIMETHICONE (300 CST); PROPYLENE GLYCOL; .ALPHA.-TOCOPHEROL ACETATE; TROLAMINE; WATER

Drug Facts

Inactive Ingredients

carbomer, fragrance, glycerin, PEG-12 dimethicone, propylene glycol, tocopheryl acetate, triethanolamine, water

Active Ingredient

Ethyl alcohol 65% v/v

Purpose

Antimicrobial

Warnings

For external use only

Flammable, keep away from fire or flame

Keep out of reach of children.

If swallowed, get medical help or contact a Poison Control Center right away

Uses

Hand sanitizer to help reduce bacteria on skin

Directions

Put a dime sized drop onto hands and rub together briskly until dry

Stop use and ask a doctor if irritation, excessive redness or rash develops

Do not use in or near the eyes. In case of contact, rinse eyes thoroughly with water

STORAGE AND HANDLING

Enter section text here Other Information

Store below 110 F (43 C)